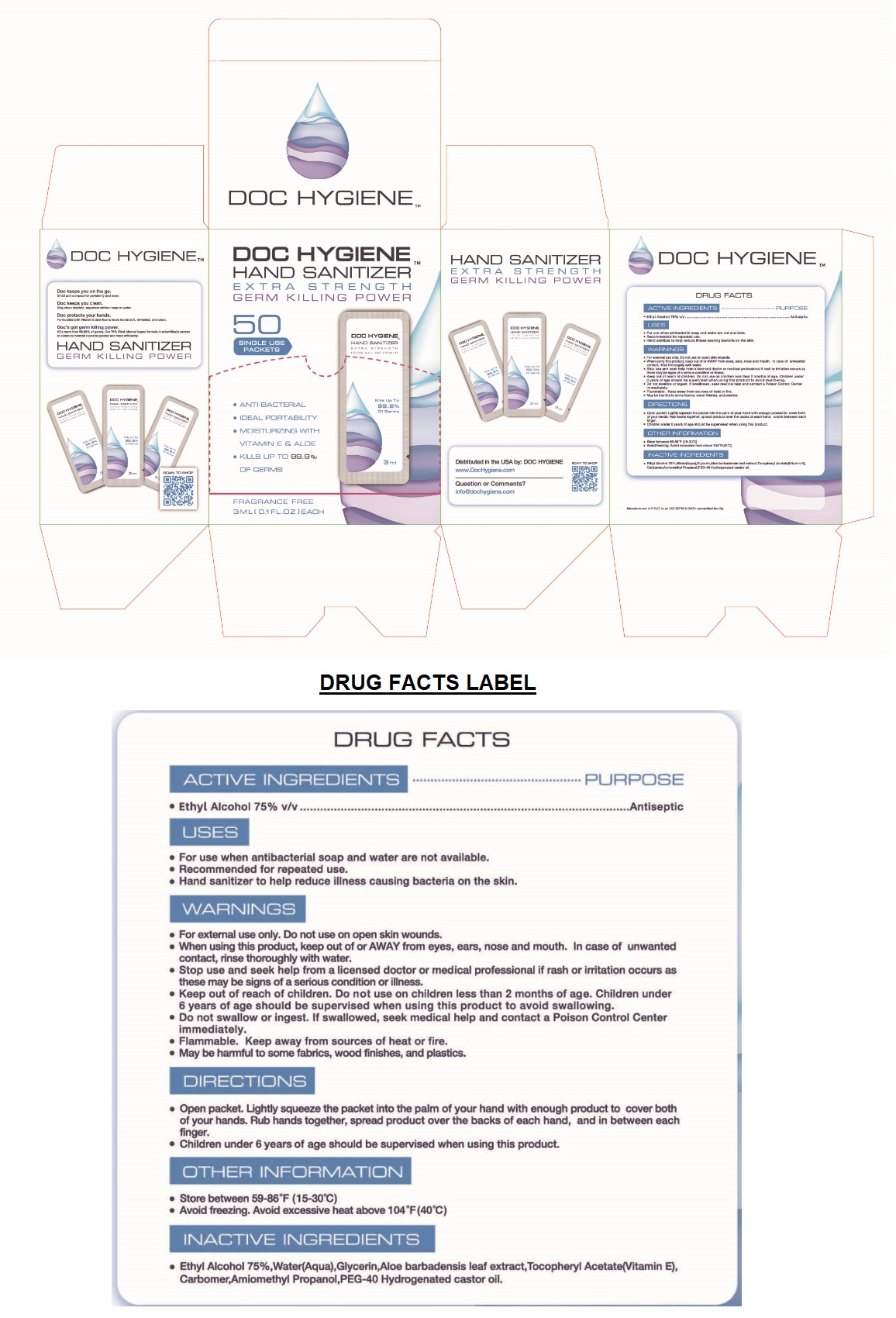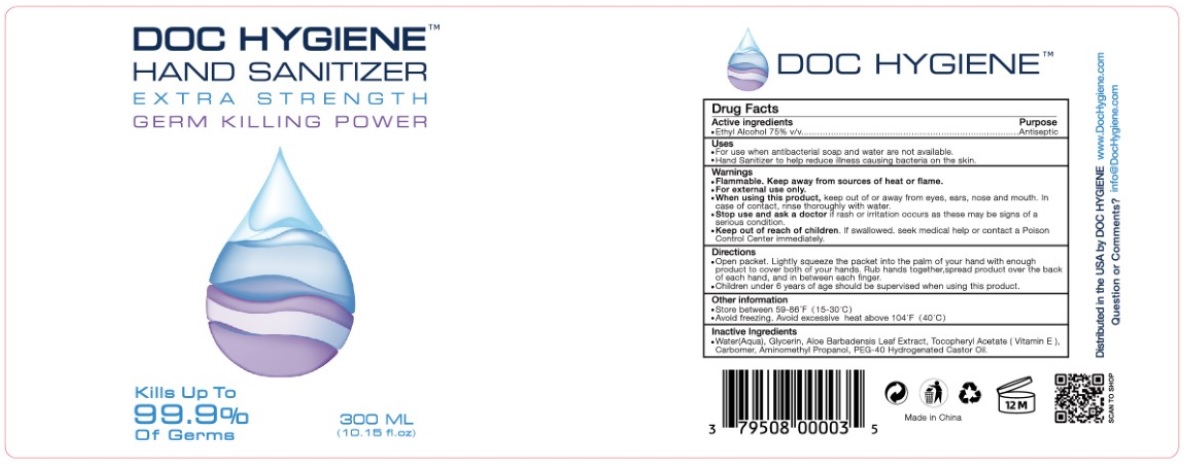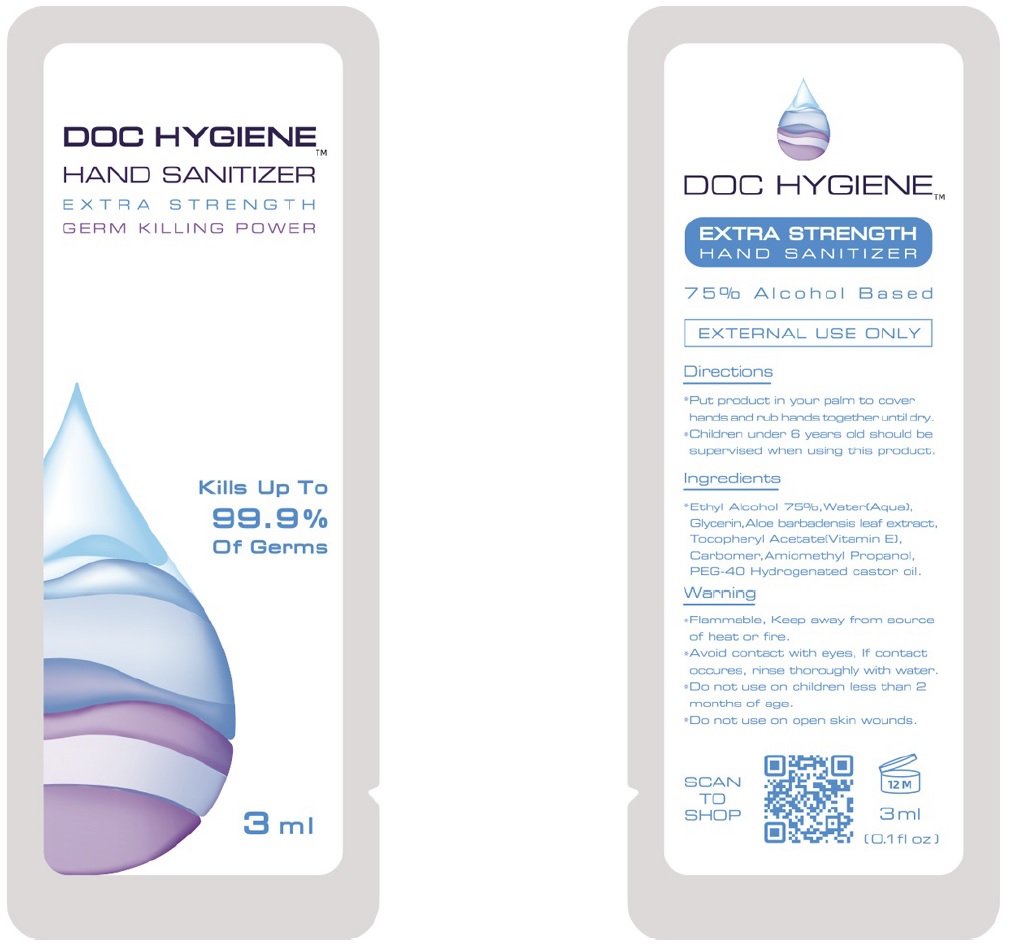 DRUG LABEL: Doc Hygiene
NDC: 79508-010 | Form: GEL
Manufacturer: Blue Flame Medical Llc
Category: otc | Type: HUMAN OTC DRUG LABEL
Date: 20200814

ACTIVE INGREDIENTS: ALCOHOL 75 mL/100 mL
INACTIVE INGREDIENTS: WATER; GLYCERIN; ALOE VERA LEAF; .ALPHA.-TOCOPHEROL ACETATE; CARBOMER HOMOPOLYMER, UNSPECIFIED TYPE; AMINOMETHYLPROPANOL; POLYOXYL 40 HYDROGENATED CASTOR OIL

DOC HYGIENE HAND SANITIZER

ACTIVE INGREDIENT

- Ethyl Alcohol 75% v/v

PURPOSE

Antiseptic

USES

- For use when antibacterial soap and water are not available.
- Recommended for repeated use.
- Hand sanitizer to help reduce illness causing bacteria on the skin.

WARNINGS

- For external use only. Do not use on open skin wounds.
- When using this product, keep out of or AWAY from eyes, ears, nose and mouth. In case of unwanted contact, rinse thoroughly with water.
- Stop use and seek help from a licensed doctor or medical professional if rash or irritation occurs as these may be signs of serious condition or illness.
- Do not swallow or ingest. If swallowed, seek medical help and contact a Poison Control Center immediately.
- Flammable. Keep away from sources of heat or fire.
- May be harmful to some fabrics, wood finishes, and plastics.

Keep out of reach of children. Do use on children less than 2 months of age. Children under 6 years of age should be supervised when using this product to avoid swallowing.

DIRECTIONS

- Open packet. Lightly squeeze the packet into the palm of your hand with enough product to cover both of your hands. Rub hands together, spread product over the backs of each hand, and in the between each finger.
- Children under 6 years of age should be supervised when using this product.

OTHER INFORMATION

- Store between 59-86°F (15-30°C)
- Avoid freezing. Avoid excessive heat above 104°F(40°C)

INACTIVE INGREDIENTS

- Water(Aqua), Glycerin, Aloe Barbadensis Leaf Extract, Tocopheryl Acetate (Vitamin E), Carbomer, Aminomethyl Propanol, PEG-40 Hydrogenated Castor Oil.

EXTRA STRENGTH

GERM KILLING POWER

- ANTI-BACTERIAL
- IDEAL PORTABILITY
- MOISTURIZING WITH VITAMIN E & ALOE
- KILLS UP TO 99.9% OF GERMS

FRAGRANCE FREE

Doc keeps you on the go.

Small and compact for portability and ease.

Doc keeps you clean.

Stay clean anytime, anywhere without soap or water.

Doc protects your hands.

Formulated with Vitamin E and Aloe to leave hands soft, refreshed, and clean.

Doc's got germ killing power.

Kills more than 99.9% of germs. Our 75% Ethyl Alcohol based formula is scientifically proven to eliminate harmful bacteria quicker and more efficiently.

Distributed in the USA by: DOC HYGIENE

www.DocHygiene.com

Question or Comments?

info@dochygiene.com

SCAN TO SHOP

Manufactured in P.R.C. in an ISO 22716 & GMPc accredited facility.